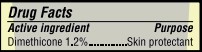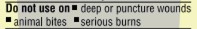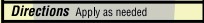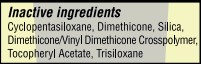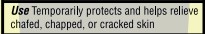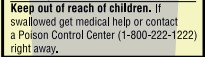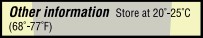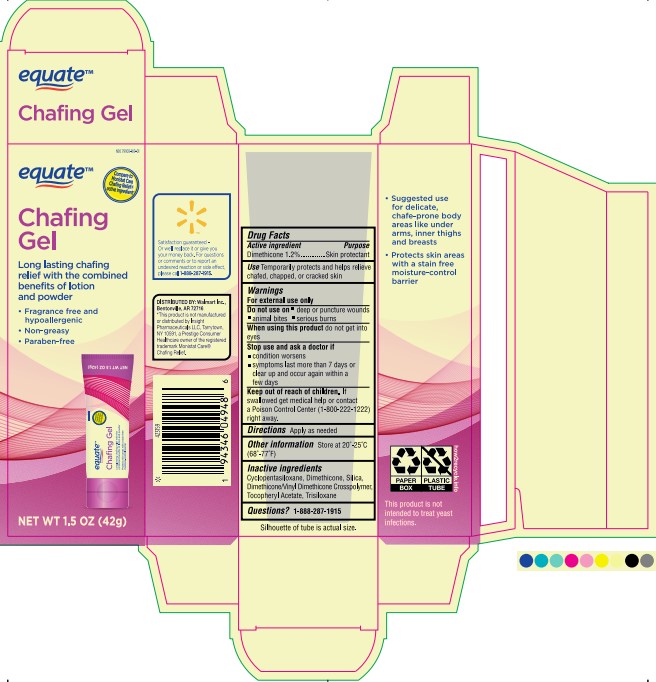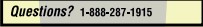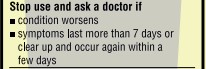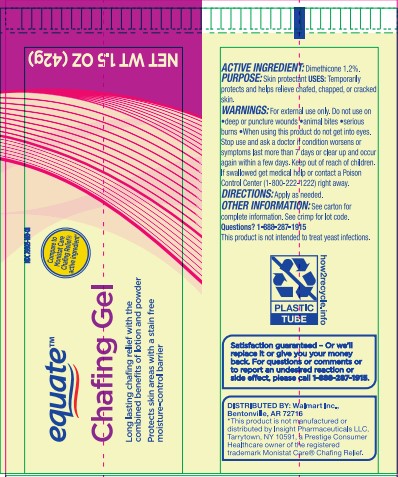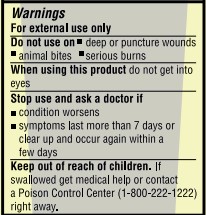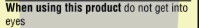 DRUG LABEL: Equate Chafing Gel
NDC: 79903-169 | Form: GEL
Manufacturer: Walmart Inc
Category: otc | Type: HUMAN OTC DRUG LABEL
Date: 20260127

ACTIVE INGREDIENTS: DIMETHICONE 200 0.504 g/42 g
INACTIVE INGREDIENTS: DIMETHICONE/VINYL DIMETHICONE CROSSPOLYMER (SOFT PARTICLE); DIMETHICONE; .ALPHA.-TOCOPHEROL ACETATE 0.000042 g/42 g; TRISILOXANE 0.000042 g/42 g; DIMETHICONE 500 0.126 g/42 g; CYCLOMETHICONE 5; SILICON DIOXIDE 1.26 g/42 g

Equate Chafing Gel 1.5oz

1: Package Quantity NDC 79903-169-01

1: Package Quantity NDC 79903-169-01